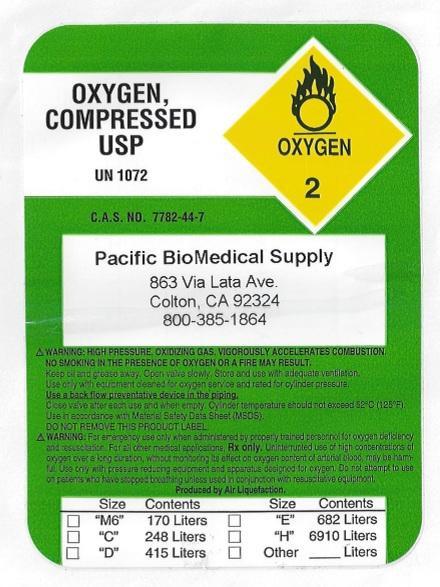 DRUG LABEL: Oxygen, Compressed
NDC: 58381-001 | Form: GAS
Manufacturer: Pulmocare Respiratory Services, Inc.
Category: prescription | Type: HUMAN PRESCRIPTION DRUG LABEL
Date: 20170221

ACTIVE INGREDIENTS: OXYGEN 1 L/1 L

Oxygen Compressed